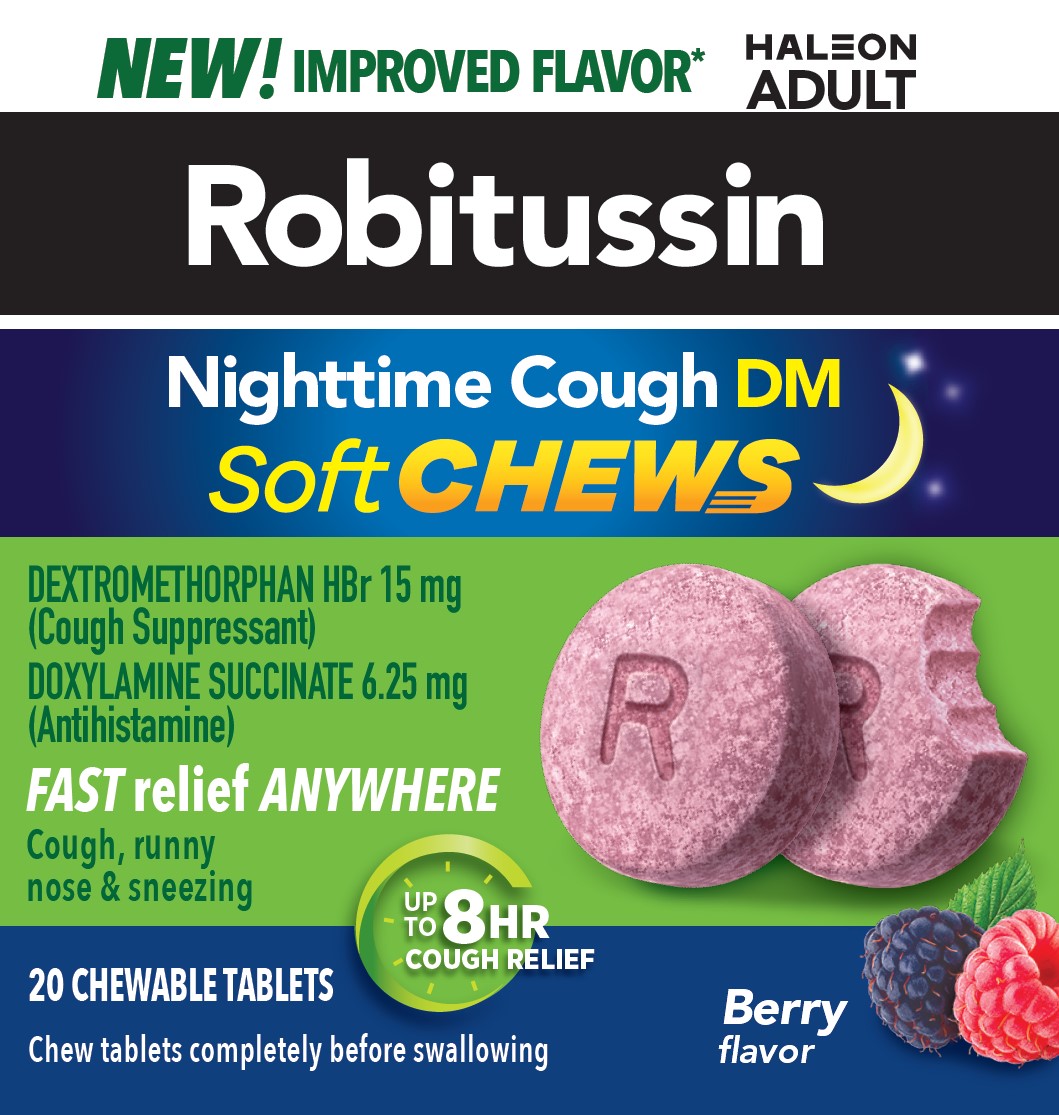 DRUG LABEL: ROBITUSSIN Nighttime Cough DM Soft CHEWS
NDC: 0031-9311 | Form: TABLET, CHEWABLE
Manufacturer: Haleon US Holdings LLC
Category: otc | Type: HUMAN OTC DRUG LABEL
Date: 20251125

ACTIVE INGREDIENTS: DEXTROMETHORPHAN HYDROBROMIDE 15 mg/1 1; DOXYLAMINE SUCCINATE 6.25 mg/1 1
INACTIVE INGREDIENTS: SUCRALOSE; SUCROSE; COW MILK; CALCIUM GLUCONATE MONOHYDRATE; CARBOXYMETHYLCELLULOSE CALCIUM; CARNAUBA WAX; CORN SYRUP; CROSPOVIDONE, UNSPECIFIED; D&C RED NO. 30 ALUMINUM LAKE; GLYCERIN; MANNITOL; STARCH, CORN; DIMETHICONE, UNSPECIFIED; SODIUM GLUCONATE; SORBITOL; SORBITOL SOLUTION

Drug Facts

Active ingredients (in each chewable tablet)

Dextromethorphan equivalent to 15 mg dextromethorphan HBr

Doxylamine succinate 6.25 mg

Purposes

Cough suppressant

Antihistamine

Uses

- temporarily relieves cough due to minor throat and bronchial irritation as may occur with a cold
- temporarily relieves these symptoms due to hay fever or other upper respiratory allergies
  - runny nose
  - sneezing
  - itchy, watery eyes
  - itching of the nose or throat
- controls the impulse to cough to help you sleep

Warnings

Do not use

- to sedate a child or to make a child sleepy
- if you are now taking a prescription monoamine oxidase inhibitor (MAOI) (certain drugs for depression, psychiatric, or emotional conditions, or Parkinson's disease), or for 2 weeks after stopping the MAOI drug. If you do not know if your prescription drug contains an MAOI, ask a doctor or pharmacist before taking this product.

Ask a doctor before use if you have

- trouble urinating due to an enlarged prostate gland
- glaucoma
- a cough that occurs with too much phlegm (mucus)
- a breathing problem or chronic cough that lasts or is chronic such as occurs with smoking, asthma, or chronic bronchitis or emphysema

Ask a doctor or pharmacist before use if you are

taking sedatives or tranquilizers

When using this product

- marked drowsiness may occur
- avoid alcoholic drinks
- alcohol, sedatives, and tranquilizers may increase drowsiness
- be careful when driving a motor vehicle or operating machinery
- excitability may occur, especially in children

Stop use and ask a doctor ifcough lasts more than 7 days, comes back, or is accompanied by fever, rash, or persistent headache. These could be signs of a serious condition.

PREGNANCY OR BREAST FEEDING

If pregnant or breast-feeding,ask a health professional before use.

Keep out of reach of children.In case of overdose, get medical help or contact a Poison Control Center right away.

Directions

- do not take more than 4 doses (8 chewable tablets) in 24-hours, unless directed by a doctor.
- chew tablets completely before swallowing
- this adult product is not intended for use in children under 12 years of age

age |  | dose
adults and children 12 years and over |  | take 2 chewable tablets every 6 hours, as needed
children under 12 years |  | do not use

Other information

- each chewable tablet contains:calcium 10 mg, potassium 10 mg, sodium 7 mg
- store at 20-25°C (68-77°F)

Inactive ingredients

calcium gluconate monohydrate, carboxymethylcellulose calcium, carnauba wax, corn syrup solids, crospovidone, D&C red no. 30 aluminum lake, FD&C blue no. 1 aluminum lake, glycerin, mannitol, natural and artificial flavors, pregelatinized starch, simethicone, sodium gluconate, sorbitol, sorbitol solution, sucralose, sucrose, whole dry milk

Questions or comments?

call weekdays from 8 AM to 6 PM EST at 1-855-297-3031

Additional Information

Do Not Use if seal under bottle cap imprinted with “SEALED for YOUR PROTECTION” is broken or missing.

*Among those with a preference vs. original formulation

PARENTS:

Learn about teen medicine abuse

www.StopMedicineabuse.org

PRINCIPAL DISPLAY PANEL

NEW!IMPROVED FLAVOR*

Robitussin

Nighttime Cough DM

Soft CHEWS

DEXTROMETHORPHAN HBr 15 mg
(Cough Suppressant)

DOXYLAMINE SUCCINATE 6.25 mg

(Antihistamine)

FAST reliefANYWHERE

Cough, runny nose & sneezing

20 CHEWABLE TABLETS

Chew tablets completely before swallowing

UP TO 8HRCOUGH RELIEF

Berry flavor